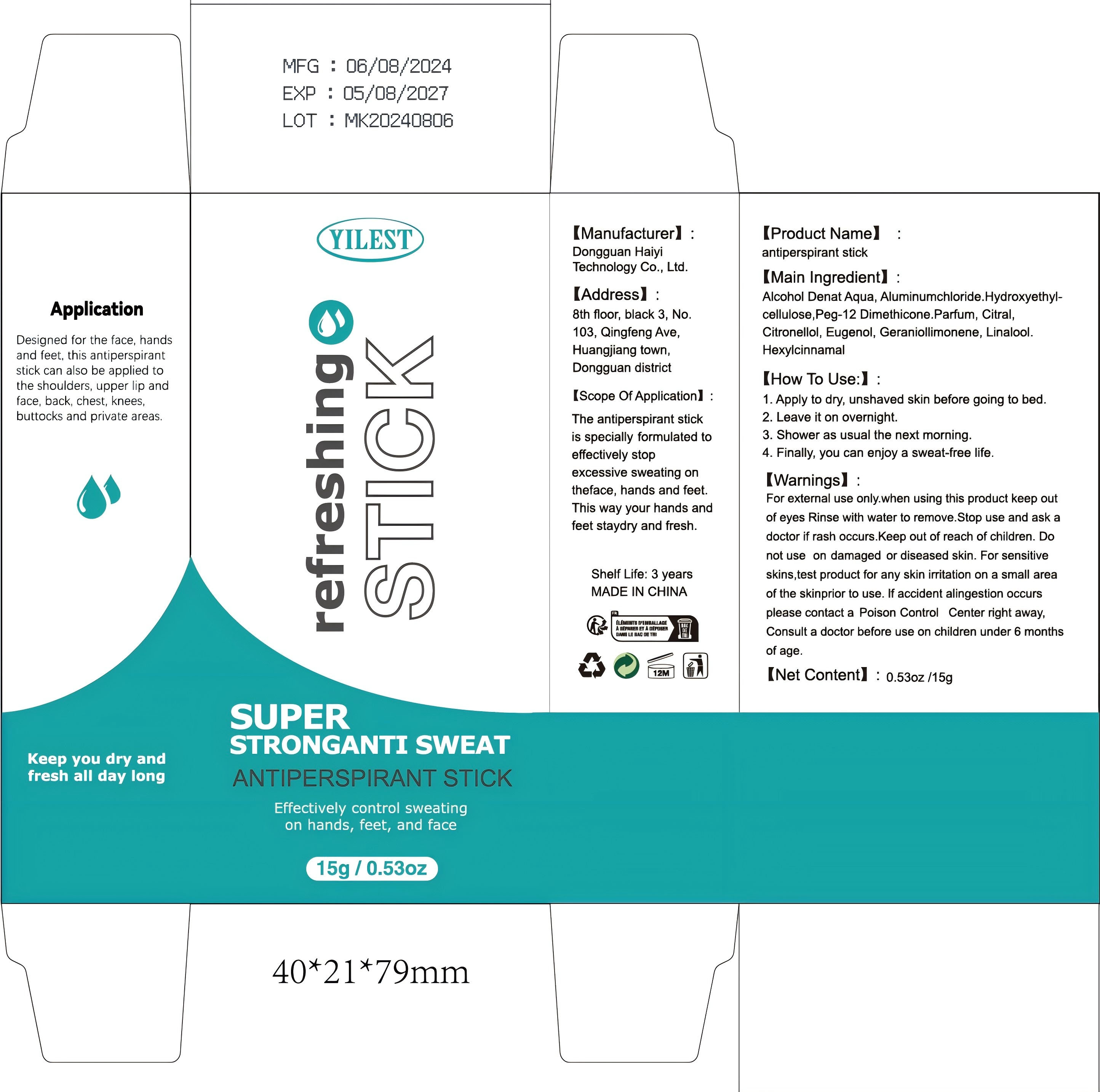 DRUG LABEL: antiperspirant stick
NDC: 84732-071 | Form: STICK
Manufacturer: Dongguan Haiyi Technology Co.,Ltd.
Category: otc | Type: HUMAN OTC DRUG LABEL
Date: 20241029

ACTIVE INGREDIENTS: ALCOHOL 1 mL/100 g
INACTIVE INGREDIENTS: HYDROXYMETHYL CELLULOSE; PARFUMIDINE; PEG-12 DIMETHICONE; EUGENOL; CITRAL; LINALOOL; ALUMINUM CHLORIDE; .ALPHA.-HEXYLCINNAMALDEHYDE; WATER; CITRONELLOL

Active ingredient

Alcohol Denat

Inactive ingredient

Aqua, Aluminumchloride，Hydroxyethyl cellulose,Peg-12 Dimethicone，Parfum, Citral,Citronellol, Eugenol, Geraniollimonene, Linalool，Hexylcinnamal

Purpose section

The antiperspirant stickis specially formulated toeffectively stopexcessive sweating ontheface, hands and feet.This way your hands andfeet staydry and fresh.

Warning

For external use only.when using this product keep out of eyes Rinse with water to remove.Stop use and ask adoctor if rash occurs.Keep out of reach of children. Donot use on damaged or diseased skin. For sensitive skins,test product for any skin iritation on a small area of the skinprior to use. lf accident alingestion occurs please contact a Poison Control Center right away,Consult a doctor before use on children under 6 months of age.

stop use

This product may cause allergic reactions in asmall number of people.
lf you experience any discomfort,please stop using it immediately.

not use

Not suitable for use by children, pregnantor breast feeding people.

OUT OF CHILDREN

KEEP THE PRODUCT OUT OF REACH OF CHILDREN to

HOW TO USE

1. Apply to dry, unshaved skin before going to bed.
2. Leave it on overnight.
3. Shower as usual the next morning.
4. Finally, you can enjoy a sweat-free life.

Dosage

Apply to dry, unshaved skin before going to bed